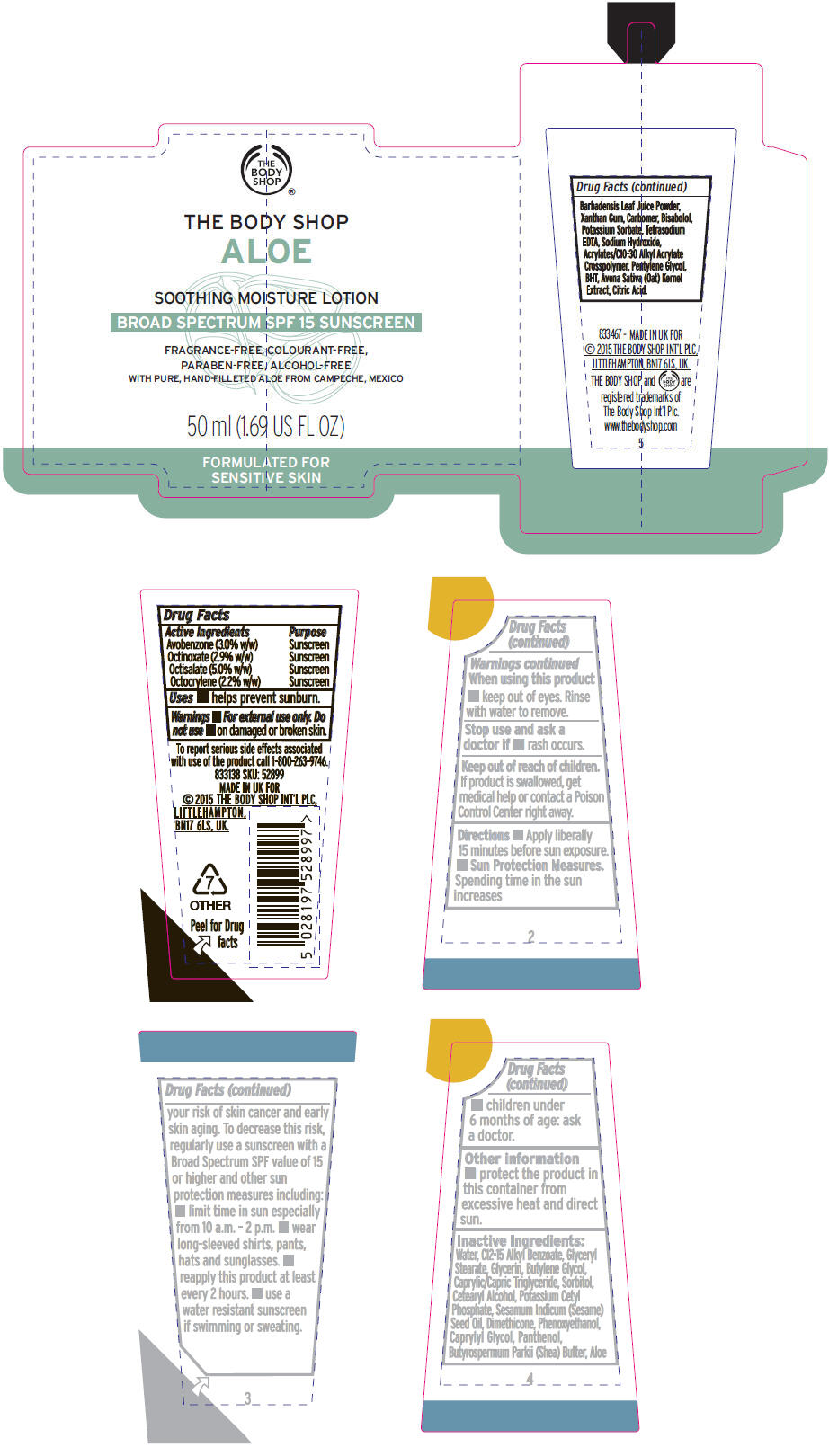 DRUG LABEL: Aloe Soothing Moisture SPF 15
NDC: 57691-889 | Form: LOTION
Manufacturer: Buth-Na-Bodhaige, Inc.,
Category: otc | Type: HUMAN OTC DRUG LABEL
Date: 20161010

ACTIVE INGREDIENTS: Octisalate 0.05 g/1 mL; Avobenzone 0.03 g/1 mL; Octinoxate 0.029 g/1 mL; Octocrylene 0.022 g/1 mL
INACTIVE INGREDIENTS: Water; Alkyl (C12-15) Benzoate; GLYCERYL MONOSTEARATE; Glycerin; Butylene Glycol; MEDIUM-CHAIN TRIGLYCERIDES; Sorbitol; Cetostearyl Alcohol; Potassium Cetyl Phosphate; SESAME OIL; Dimethicone; Phenoxyethanol; Caprylyl Glycol; Panthenol; SHEA BUTTER; ALOE VERA LEAF; Xanthan Gum; CARBOMER INTERPOLYMER TYPE A (ALLYL SUCROSE CROSSLINKED); LEVOMENOL; Potassium Sorbate; EDETATE SODIUM; Sodium Hydroxide; Pentylene Glycol; BUTYLATED HYDROXYTOLUENE; OAT; CITRIC ACID MONOHYDRATE

Aloe Soothing Moisture Lotion SPF 15

Drug Facts

ACTIVE INGREDIENT

Active Ingredients | Purpose
Avobenzone (3.0% w/w) | Sunscreen
Octinoxate (2.9% w/w) | Sunscreen
Octisalate (5.0% w/w) | Sunscreen
Octocrylene (2.2% w/w) | Sunscreen

Uses

- helps prevent sunburn.

Warnings

- For external use only.

Do not use

- on damaged or broken skin.

When using this product

- keep out of eyes. Rinse with water to remove.

Stop use and ask a doctor if

- rash occurs.

Keep out of reach of children.

If product is swallowed, get medical help or contact a Poison Control Center right away.

Directions

- Apply liberally 15 minutes before sun exposure.
- Sun Protection Measures.
  Spending time in the sun increases your risk of skin cancer and early skin aging. To decrease this risk, regularly use a sunscreen with a Broad Spectrum SPF value of 15 or higher and other sun protection measures including:
  - limit time in sun especially from 10 a.m. – 2 p.m.
  - wear long-sleeved shirts, pants, hats and sunglasses.
  - reapply this product at least every 2 hours.
  - use a water resistant sunscreen if swimming or sweating.
- children under 6 months of age: ask a doctor.

Other information

- protect the product in this container from excessive heat and direct sun.

Inactive Ingredients

Water, C12-15 Alkyl Benzoate, Glyceryl Stearate, Glycerin, Butylene Glycol, Caprylic/Capric Triglyceride, Sorbitol, Cetearyl Alcohol, Potassium Cetyl Phosphate, Sesamum Indicum (Sesame) Seed Oil, Dimethicone, Phenoxyethanol, Caprylyl Glycol, Panthenol, Butyrospermum Parkii (Shea) Butter, Aloe Barbadensis Leaf Juice Powder, Xanthan Gum, Carbomer, Bisabolol, Potassium Sorbate, Tetrasodium EDTA, Sodium Hydroxide, Acrylates/C10-30 Alkyl Acrylate Crosspolymer, Pentylene Glycol, BHT, Avena Sativa (Oat) Kernel Extract, Citric Acid.

PRINCIPAL DISPLAY PANEL - 50 ml Tube Label

THE
BODY
SHOP

THE BODY SHOP
ALOE

SOOTHING MOISTURE LOTION

BROAD SPECTRUM SPF 15 SUNSCREEN

FRAGRANCE-FREE, COLOURANT-FREE,
PARABEN-FREE, ALCOHOL-FREE
WITH PURE, HAND-FILLETED ALOE FROM CAMPECHE, MEXICO

50 ml (1.69 US FL OZ)

FORMULATED FOR
SENSITIVE SKIN